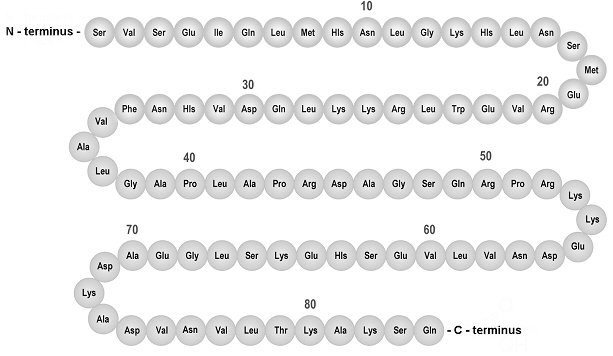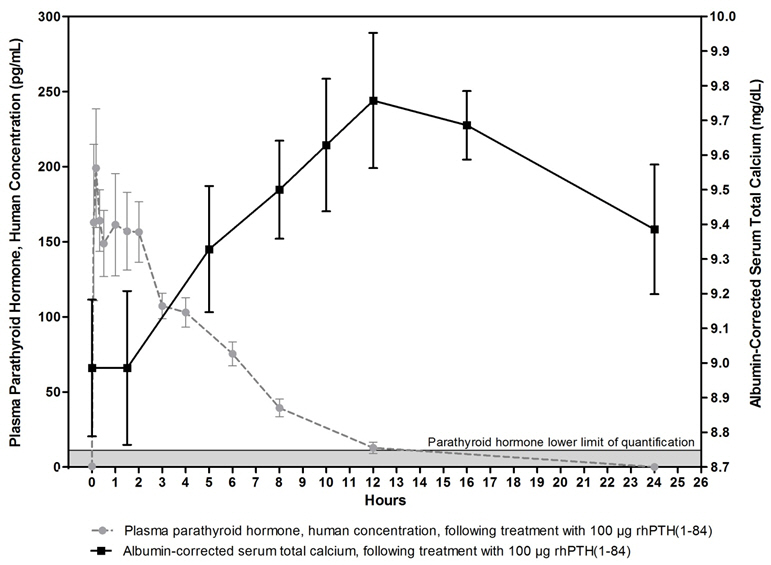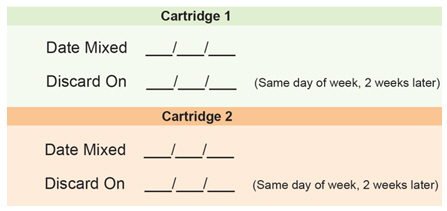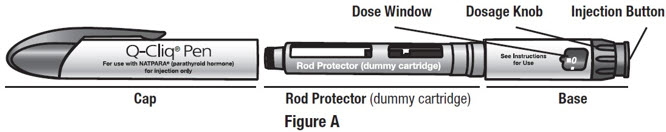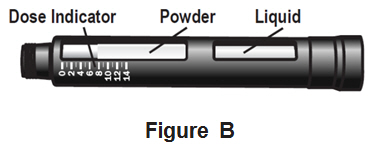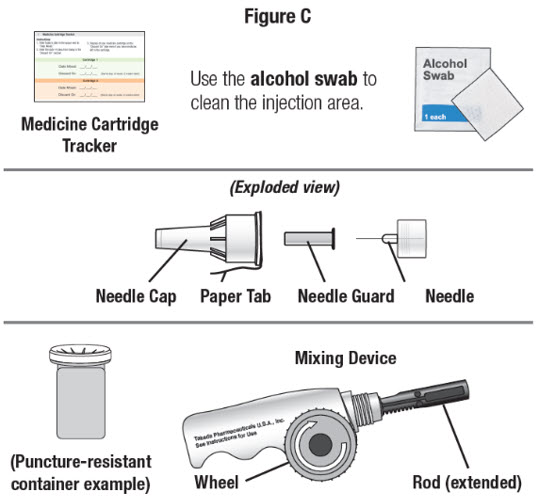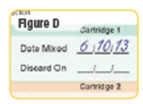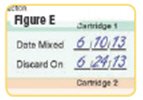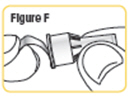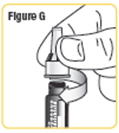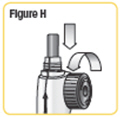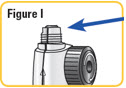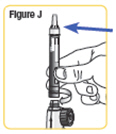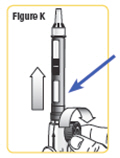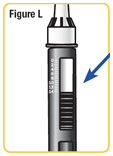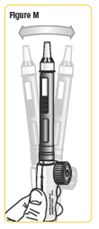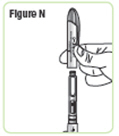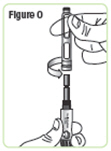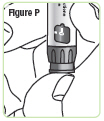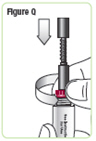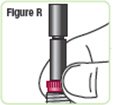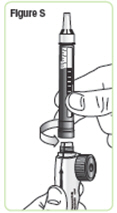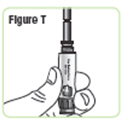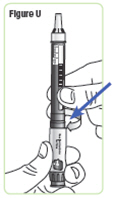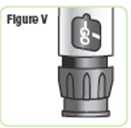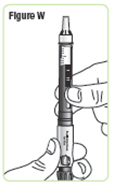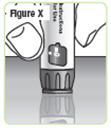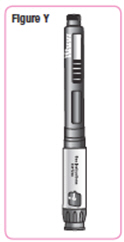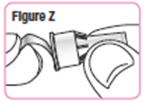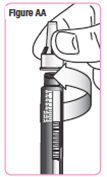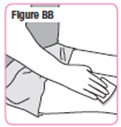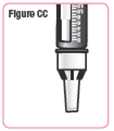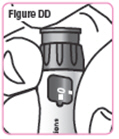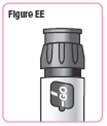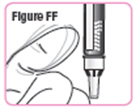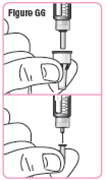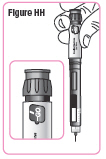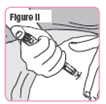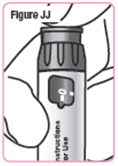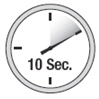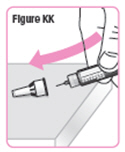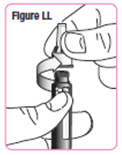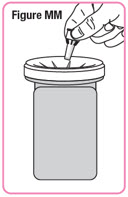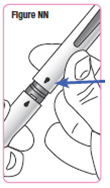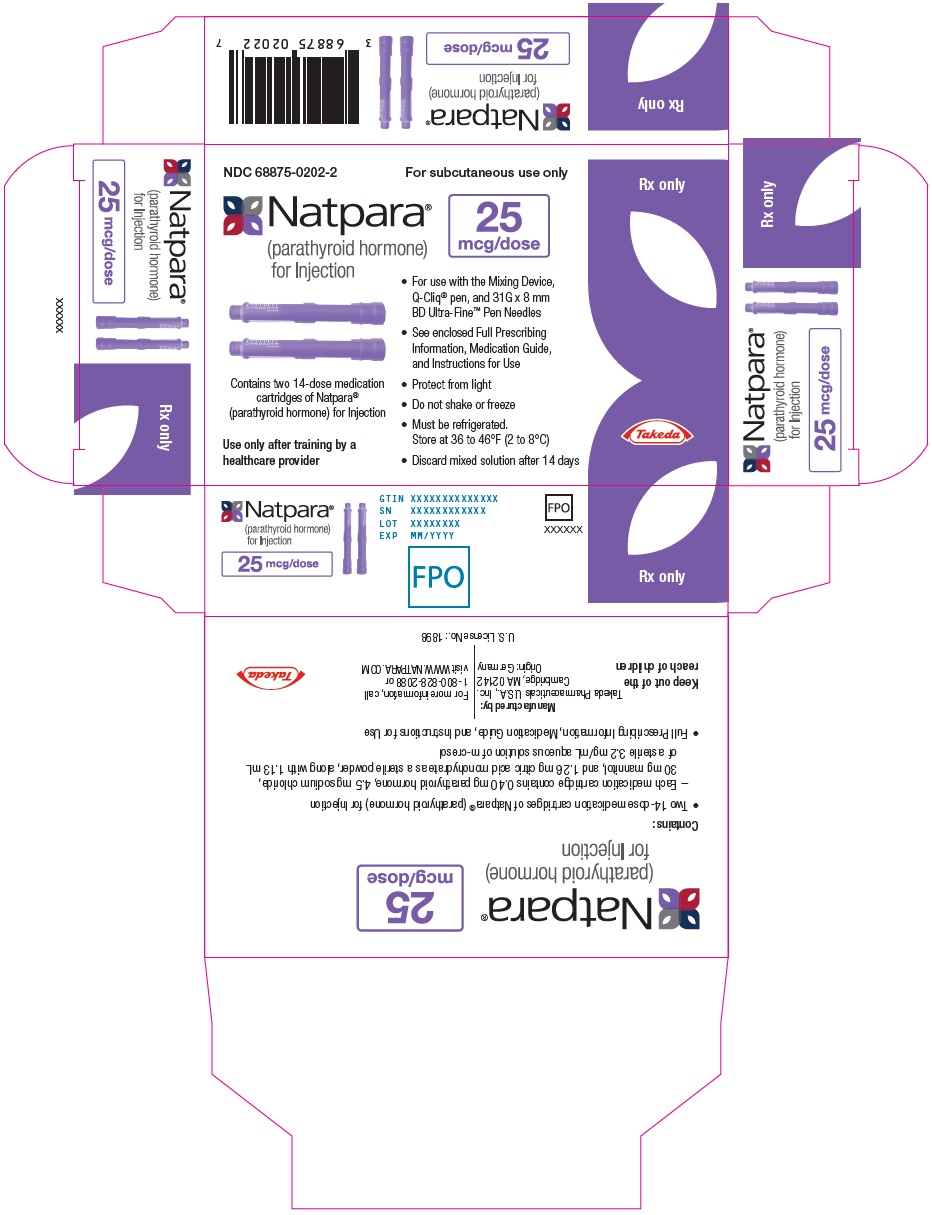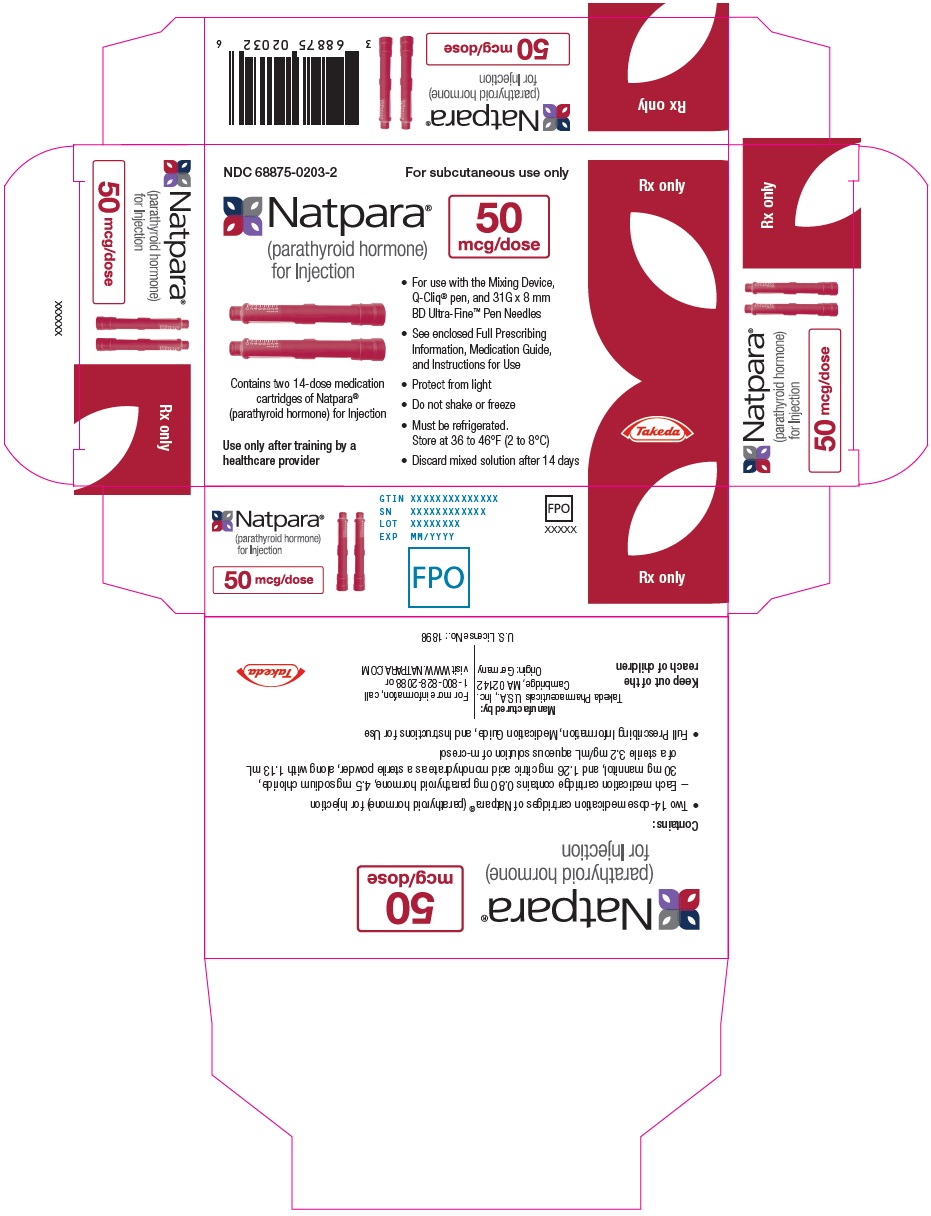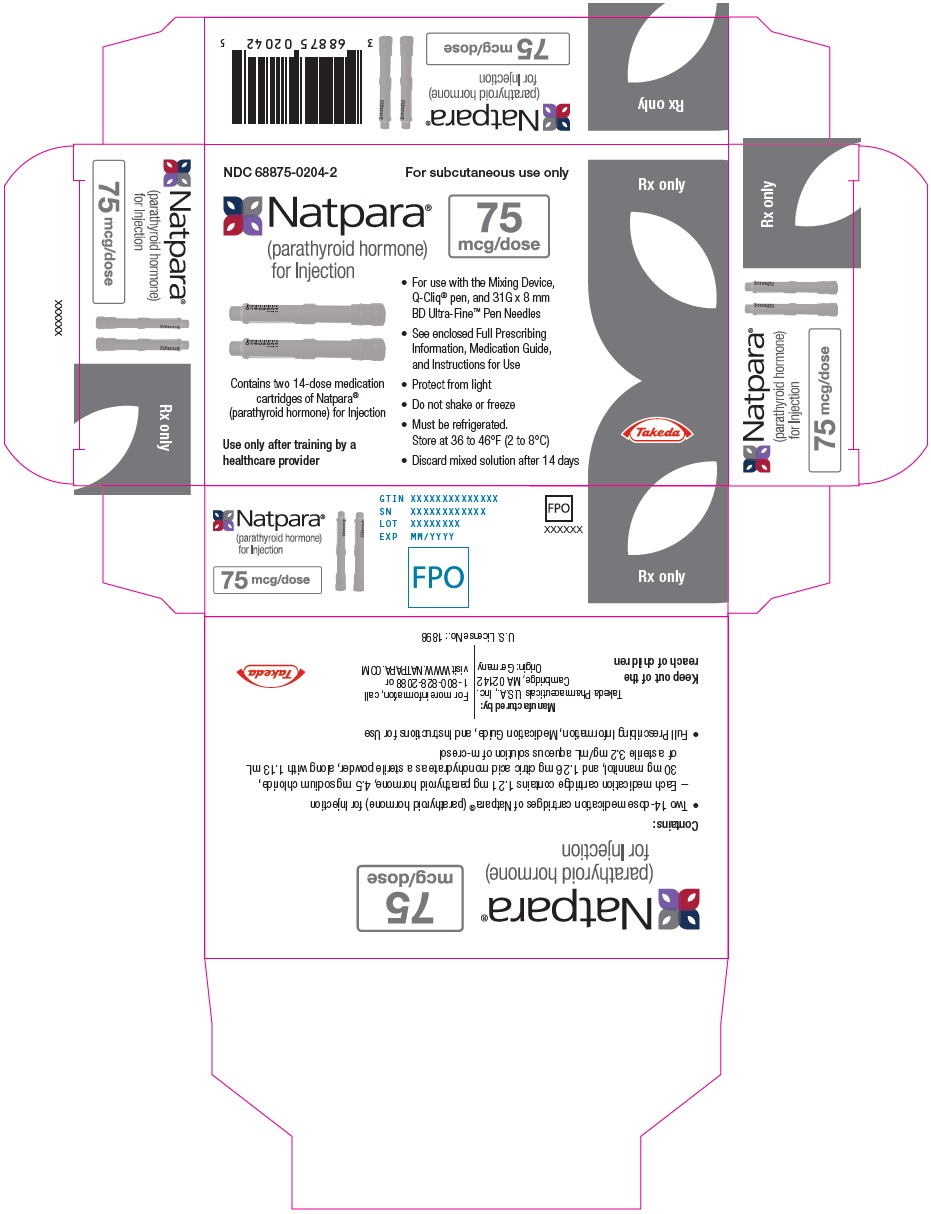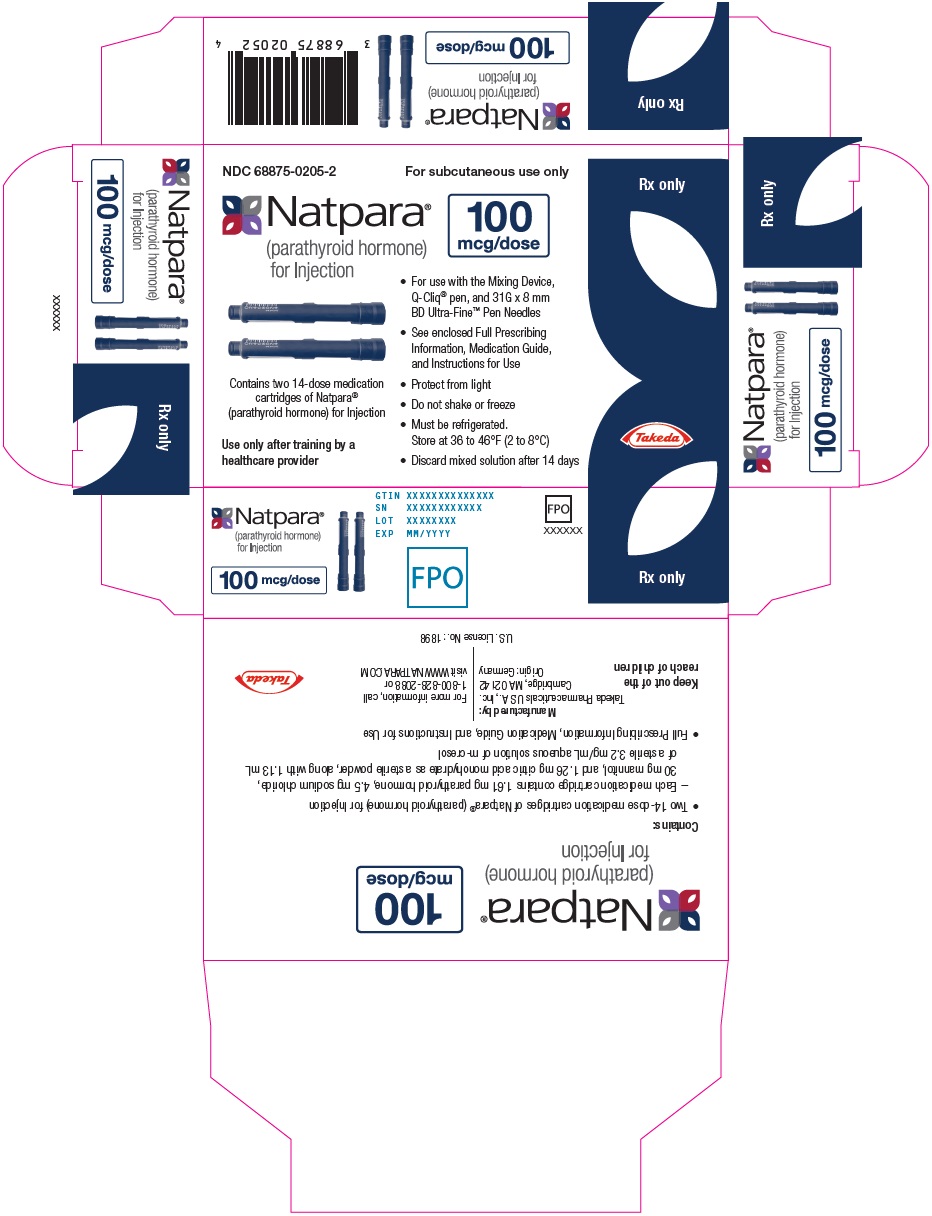 DRUG LABEL: NATPARA (parathyroid hormone)
NDC: 68875-0202 | Form: INJECTION, POWDER, LYOPHILIZED, FOR SOLUTION
Manufacturer: Takeda Pharmaceuticals America, Inc.
Category: prescription | Type: HUMAN PRESCRIPTION DRUG LABEL
Date: 20250711

ACTIVE INGREDIENTS: parathyroid hormone 25 ug/0.08 mL
INACTIVE INGREDIENTS: MANNITOL; SODIUM CHLORIDE; CITRIC ACID MONOHYDRATE; WATER; METACRESOL

HIGHLIGHTS OF PRESCRIBING INFORMATION

These highlights do not include all the information needed to use NATPARA safely and effectively. See full prescribing information for NATPARA.
NATPARA® (parathyroid hormone) for injection, for subcutaneous use
Initial U.S. Approval: 2015

WARNING: POTENTIAL RISK OF OSTEOSARCOMA

See full prescribing information for complete boxed warning.

- In male and female rats, parathyroid hormone caused an increase in the incidence of osteosarcoma (a malignant bone tumor) that was dependent on dose and treatment duration. A risk to humans could not be excluded (5.1, 13.1)
- Because of the potential risk of osteosarcoma, prescribe NATPARA only to patients who cannot be well-controlled on calcium and active forms of vitamin D and for whom the potential benefits are considered to outweigh the potential risk. (1, 5.1)
- Avoid use of NATPARA in patients who are at increased baseline risk for osteosarcoma (including those with Paget's disease of bone or unexplained elevations of alkaline phosphatase, pediatric and young adult patients with open epiphyses, patients with hereditary disorders predisposing to osteosarcoma or patients with a history of prior external beam or implant radiation therapy involving the skeleton) (5.1)
- NATPARA is available only through a restricted program called the NATPARA REMS Program (5.2)

1 INDICATIONS AND USAGE

NATPARA is a parathyroid hormone indicated as an adjunct to calcium and vitamin D to control hypocalcemia in patients with hypoparathyroidism. (1)

Limitations of Use

- Because of the potential risk of osteosarcoma, NATPARA is recommended only for patients who cannot be well-controlled on calcium supplements and active forms of vitamin D alone. (5.1)
- NATPARA was not studied in patients with hypoparathyroidism caused by calcium-sensing receptor mutations.
- NATPARA was not studied in patients with acute post-surgical hypoparathyroidism.

2 DOSAGE AND ADMINISTRATION

- The dose of NATPARA should be individualized to achieve a serum calcium level in the lower half of the normal range. (2.1)
- Confirm vitamin D stores are sufficient and serum calcium is above 7.5 mg/dL before starting NATPARA. (2.2)
- The starting dose of NATPARA is 50 mcg injected once daily in the thigh. When starting NATPARA, decrease dose of active vitamin D by 50%, if serum calcium is above 7.5 mg/dL. (2.3)
- Monitor serum calcium levels every 3 to 7 days after starting or adjusting NATPARA dose and when adjusting either active vitamin D or calcium supplements dose while using NATPARA. (2.1, 5.3, 5.4)

3 DOSAGE FORMS AND STRENGTHS

NATPARA is supplied as a multiple-dose, dual-chamber glass cartridge containing a sterile lyophilized powder and a sterile diluent for reconstitution in four dosage strengths. (3)

For injection: 25 mcg, 50 mcg, 75 mcg, or 100 mcg. (3)

4 CONTRAINDICATIONS

Hypersensitivity to any component of this product. (4)

5 WARNINGS AND PRECAUTIONS

- Potential Risk of Osteosarcoma: Prescribe NATPARA only to patients who cannot be well-controlled on calcium and active vitamin D. Avoid use of NATPARA in patients who are at increased risk for osteosarcoma. (5.1)
- Severe Hypercalcemia: Monitor serum calcium when starting or adjusting NATPARA dose and when making changes to co-administered drugs known to raise serum calcium. (2.4, 5.3, 6.1)
- Severe Hypocalcemia: Can occur with interruption or discontinuation of NATPARA treatment. Monitor serum calcium and replace calcium and vitamin D. (2.4, 5.4, 6.1)
- Digoxin Toxicity: Hypercalcemia increases the risk of digoxin toxicity. In patients using NATPARA concomitantly with digoxin, monitor serum calcium more frequently and increase monitoring when initiating or adjusting NATPARA dose. (5.5)
- Hypersensitivity: Hypersensitivity reactions (anaphylaxis, dyspnea, angioedema, urticaria, rash) have been reported. If signs or symptoms of a serious hypersensitivity reaction occur, discontinue treatment with NATPARA and treat patient according to the standard of care (2.6, 4, 5.6, 6.3)

6 ADVERSE REACTIONS

- The most common adverse reactions associated with NATPARA and occurring in greater than 10% of individuals were: paresthesia, hypocalcemia, headache, hypercalcemia, nausea, hypoesthesia, diarrhea, vomiting, arthralgia, hypercalciuria and pain in extremity (6.1)

To report SUSPECTED ADVERSE REACTIONS, contact Takeda Pharmaceuticals at 1-800-828-2088 or FDA at 1-800-FDA-1088 or www.fda.gov/medwatch.

7 DRUG INTERACTIONS

- Digoxin: Monitor serum calcium more frequently when using NATPARA in patients receiving digoxin. (5.5, 7.2)

8 USE IN SPECIFIC POPULATIONS

- Lactation: Monitor infants exposed to parathyroid hormone through breast milk for symptoms of hypercalcemia or hypocalcemia. Monitoring of serum calcium in the infant should be considered (8.2).
- The safety and efficacy in pediatric patients have not been established. (8.4)
- No dose adjustment is recommended in patients ≥65 years of age, or in patients with mild to moderate renal or hepatic impairment. (2.4, 8.5, 8.6, 12.3)

FULL PRESCRIBING INFORMATION

WARNING: POTENTIAL RISK OF OSTEOSARCOMA

- In male and female rats, parathyroid hormone caused an increase in the incidence of osteosarcoma (a malignant bone tumor). The occurrence of osteosarcoma was dependent on parathyroid hormone dose and treatment duration. This effect was observed at parathyroid hormone exposure levels ranging from 3 to 71 times the exposure levels in humans receiving a 100 mcg dose of NATPARA. These data could not exclude a risk to humans [see Warnings and Precautions (5.1), Nonclinical Toxicology (13.1)].
- Because of a potential risk of osteosarcoma, use NATPARA only in patients who cannot be well-controlled on calcium and active forms of vitamin D alone and for whom the potential benefits are considered to outweigh this potential risk [see Indications and Usage (1), Warnings and Precautions (5.1)].
- Avoid use of NATPARA in patients who are at increased baseline risk for osteosarcoma, such as patients with Paget's disease of bone or unexplained elevations of alkaline phosphatase, pediatric and young adult patients with open epiphyses, patients with hereditary disorders predisposing to osteosarcoma or patients with a prior history of external beam or implant radiation therapy involving the skeleton [see Warnings and Precautions (5.1)].
- Because of the risk of osteosarcoma, NATPARA is available only through a restricted program under a Risk Evaluation and Mitigation Strategy (REMS) called the NATPARA REMS Program [see Warnings and Precautions (5.2)].

1 INDICATIONS AND USAGE

NATPARA is a parathyroid hormone indicated as an adjunct to calcium and vitamin D to control hypocalcemia in patients with hypoparathyroidism.

Limitations of Use

- Because of the potential risk of osteosarcoma, NATPARA is recommended only for patients who cannot be well-controlled on calcium supplements and active forms of vitamin D alone [see Warnings and Precautions (5.1)].
- NATPARA was not studied in patients with hypoparathyroidism caused by calcium-sensing receptor mutations.
- NATPARA was not studied in patients with acute post-surgical hypoparathyroidism.

2 DOSAGE AND ADMINISTRATION

2.1 Dosing Guidelines

The dose of NATPARA should be individualized based on total serum calcium (albumin-corrected) and 24-hour urinary calcium excretion. The recommended NATPARA dose is the minimum dose required to prevent both hypocalcemia and hypercalciuria. This dose will generally be the dose that maintains total serum calcium (albumin-corrected) within the lower half of the normal range (i.e., between 8 and 9 mg/dL) without the need for active forms of vitamin D and with calcium supplementation sufficient and individualized to meet the patient's daily requirements.

Doses of active forms of vitamin D and calcium supplements will need to be adjusted when using NATPARA.

2.2 Before Initiating NATPARA and During Therapy with NATPARA

- Confirm 25-hydroxyvitamin D stores are sufficient. If insufficient, replace to sufficient levels per standard of care.
- Confirm serum calcium is above 7.5 mg/dL before starting NATPARA.
- The goal of NATPARA treatment is to achieve serum calcium within the lower half of the normal range.

2.3 Initiating NATPARA

1. Initiate NATPARA 50 mcg once daily as a subcutaneous injection in the thigh (alternate thigh every day).
2. In patients using active forms of vitamin D, decrease the dose of active vitamin D by 50%, if serum calcium is above 7.5 mg/dL.
3. In patients using calcium supplements, maintain calcium supplement dose.
4. Measure serum calcium concentration within 3 to 7 days.
5. Adjust dose of active vitamin D or calcium supplement or both based on serum calcium value and clinical assessment (i.e., signs and symptoms of hypocalcemia or hypercalcemia). Suggested adjustments to active vitamin D and calcium supplement based on serum calcium levels are provided below (see Table 1).

Table 1: Recommended Dosage Adjustments for NATPARA
 | Adjust First | Adjust Second
Serum Calcium | Active Vitamin D Forms | Calcium Supplement
Above the Upper Limit of Normal (10.6 mg/dL) | Decrease or Discontinue [Discontinue in patients receiving the lowest available dose] | Decrease
Greater than 9 mg/dL and below the Upper Limit of Normal (10.6 mg/dL) | Decrease or Discontinue | No change or decrease if active vitamin D has been discontinued
Less than or equal to 9 mg/dL and above 8 mg/dL | No change | No change
Lower than 8 mg/dL | Increase | Increase

6. Repeat steps 4 and 5 until target serum calcium levels are within the lower half of the normal range, active vitamin D has been discontinued and calcium supplementation is sufficient to meet daily requirements.

2.4 NATPARA Dose Adjustments

The dose of NATPARA may be increased in increments of 25 mcg every four weeks up to a maximum daily dose of 100 mcg if serum calcium cannot be maintained above 8 mg/dL without an active form of vitamin D and/or oral calcium supplementation.

The dose of NATPARA may be decreased to as low as 25 mcg per day if total serum calcium is repeatedly above 9 mg/dL after the active form of vitamin D has been discontinued and calcium supplement has been decreased to a dose sufficient to meet daily requirements.

After a NATPARA dose change monitor clinical response as well as serum calcium. Adjust active vitamin D and calcium supplements per steps 4-6 above if indicated [see Dosage and Administration (2.3)].

2.5 NATPARA Maintenance Dose

The maintenance dose should be the lowest dose that achieves a total serum calcium (albumin-corrected) within the lower half of the normal total serum calcium range (i.e., approximately 8 and 9 mg/dL), without the need for active forms of vitamin D and with calcium supplementation sufficient to meet daily requirements. Monitor serum calcium and 24-hour urinary calcium per standard of care once a maintenance dose is achieved.

2.6 NATPARA Dose Interruption or Discontinuation

Abrupt interruption or discontinuation of NATPARA can result in severe hypocalcemia. Resume treatment with, or increase the dose of, an active form of vitamin D and calcium supplements if indicated in patients interrupting or discontinuing NATPARA, monitor for signs and symptoms of hypocalcemia and serum calcium levels [see Warnings and Precautions (5.4)].

In the case of a missed dose, the next NATPARA dose should be administered as soon as reasonably feasible and additional exogenous calcium should be taken in the event of hypocalcemia.

2.7 Reconstitution and Administration Instructions

- Patients and caregivers who will administer NATPARA should receive appropriate training and instruction by a trained healthcare professional prior to first use of NATPARA.
- Follow the Instructions for Use to reconstitute NATPARA using the mixing device for reconstitution and to administer NATPARA using the pen delivery device (i.e., Q-Cliq® pen).
- Inspect NATPARA visually for particulate matter and discoloration prior to administration.
- Discard the needle in a puncture-resistant container following administration.
- Store the Q-Cliq pen containing the remaining doses of NATPARA in a refrigerator.
- All reconstituted NATPARA medication cartridges older than 14 days must be discarded [see How Supplied/Storage and Handling (16.2)].

3 DOSAGE FORMS AND STRENGTHS

NATPARA is supplied as a multiple-dose, dual-chamber glass cartridge containing a sterile powder and diluent in 4 dosage strengths.

For injection: | 25 mcg per dose strength | (0.4 mg for reconstitution with 1.13 mL)
For injection: | 50 mcg per dose strength | (0.8 mg for reconstitution with 1.13 mL)
For injection: | 75 mcg per dose strength | (1.21 mg for reconstitution with 1.13 mL)
For injection: | 100 mcg per dose strength | (1.61 mg for reconstitution with 1.13 mL)

4 CONTRAINDICATIONS

NATPARA is contraindicated in patients with a known hypersensitivity to any component of this product. Hypersensitivity reactions (e.g., anaphylaxis, angioedema, and urticaria) have occurred with NATPARA [see Warnings and Precautions (5.6), Adverse Reactions (6.3)].

5 WARNINGS AND PRECAUTIONS

5.1 Potential Risk of Osteosarcoma

In male and female rats, parathyroid hormone caused an increase in the incidence of osteosarcoma (a malignant bone tumor). The occurrence of osteosarcoma was observed to be dependent on parathyroid hormone dose and treatment duration. This effect was observed at parathyroid hormone exposure levels ranging from 3 to 71 times the exposure levels for humans receiving a 100 mcg dose of NATPARA. These data could not exclude a risk to humans [see Nonclinical Toxicology (13.1)].

Because of a potential risk of osteosarcoma, use NATPARA only in patients who cannot be well-controlled on calcium supplements and active forms of vitamin D alone and for whom the potential benefits are considered to outweigh this potential risk [see Limitations of Use (1)].

To further mitigate the potential risk of osteosarcoma, avoid use of NATPARA in patients who are at increased risk for osteosarcoma, such as patients with Paget's disease of bone or unexplained elevations of alkaline phosphatase, pediatric and young adult patients with open epiphyses, patients with hereditary disorders predisposing to osteosarcoma, or patients with a prior history of external beam or implant radiation therapy involving the skeleton. Instruct patients to promptly report clinical symptoms (e.g., persistent localized pain) and signs (e.g., soft tissue mass tender to palpation) that could be consistent with osteosarcoma.

NATPARA is available only through a restricted program under a REMS [see Warnings and Precautions (5.2)].

5.2 NATPARA REMS Program

Because of the potential risk of osteosarcoma associated with NATPARA therapy, NATPARA is available only through a restricted REMS program called the NATPARA REMS Program. Under the NATPARA REMS Program, only certified healthcare providers can prescribe and only certified pharmacies can dispense NATPARA. Further information is available at www.NATPARAREMS.com or by telephone at 1-855-NATPARA (1-855-628-7272).

5.3 Hypercalcemia

Severe hypercalcemia has been reported with NATPARA. In the pivotal trial, 3 patients randomized to NATPARA required administration of IV fluids to correct hypercalcemia during treatment with NATPARA. The risk is highest when starting or increasing the dose of NATPARA, but can occur at any time. Monitor serum calcium and patients for signs and symptoms of hypercalcemia. Treat hypercalcemia per standard practice and consider holding and/or lowering the dose of NATPARA if severe hypercalcemia occurs [see Dosage and Administration (2), Adverse Reactions (6.1)].

5.4 Hypocalcemia

Severe hypocalcemia has been reported in patients taking NATPARA, including cases of hypocalcemia that resulted in seizures. The risk is highest when NATPARA is withheld, missed or abruptly discontinued, but can occur at any time. Monitor serum calcium and patients for signs and symptoms of hypocalcemia. Resume treatment with, or increase the dose of, an active form of vitamin D or calcium supplements or both if indicated in patients interrupting or discontinuing NATPARA to prevent severe hypocalcemia [see Dosage and Administration (2.6), Adverse Reactions (6.1)].

5.5 Risk of Digoxin Toxicity with Concomitant Use of Digitalis Compounds

The inotropic effects of digoxin are affected by serum calcium levels. Hypercalcemia of any cause may predispose to digoxin toxicity. In patients using NATPARA concomitantly with digitalis compounds, monitor serum calcium and digoxin levels and patients for signs and symptoms of digitalis toxicity. Adjustment of digoxin and/or NATPARA may be needed. No drug-drug interaction study has been conducted with digoxin and NATPARA [see Drug Interactions (7), Adverse Reactions (6.1)].

5.6 Hypersensitivity

There have been reports of hypersensitivity reactions in patients taking NATPARA. Reactions included anaphylaxis, dyspnea, angioedema, urticaria, and rash. If signs or symptoms of a serious hypersensitivity reaction occur, discontinue treatment with NATPARA, treat hypersensitivity reaction according to the standard of care, and monitor until signs and symptoms resolve [see Contraindications (4), Adverse Reactions (6.3)]. Monitor for hypocalcemia if NATPARA is discontinued [see Dosage and Administration (2.6)].

6 ADVERSE REACTIONS

The following serious adverse reactions are described in greater detail in other sections of the label:

- Osteosarcoma [see Boxed Warning, Warnings and Precautions (5.1)]
- Hypercalcemia [see Warnings and Precautions (5.3)]
- Hypocalcemia [see Warnings and Precautions (5.4)]
- Hypersensitivity [see Contraindications (4), Warnings and Precautions (5.6)]

6.1 Adverse Reactions in Clinical Trials for Hypoparathyroidism

Because clinical trials are conducted under widely varying conditions, the adverse reaction rates observed cannot be directly compared to rates in other clinical trials and may not reflect the rates observed in clinical practice.

NATPARA was studied in a placebo-controlled trial [see Clinical Studies (14)].

The data described in Table 2 below reflect exposure to NATPARA in 84 patients, including 78 exposed for 24 weeks. The mean age of the trial population was 47 years and ranged from 19 to 74 years old. Seventy-nine percent (79%) were females. Ninety-six percent (96%) were Caucasian, 0.8% were Black, and 1.6% were Asian. Patients had had hypoparathyroidism for on average 15 years and hypoparathyroidism was caused by post-surgical complications in 71% of cases, idiopathic hypoparathyroidism in 25% of cases, DiGeorge Syndrome in 3% of cases, and auto-immune hypoparathyroidism in 1% of cases. Prior to trial enrollment, participants were receiving a median (interquartile range) daily oral calcium dose of 2000 (1250, 3000) mg and a median daily oral active vitamin D dose equivalent to 0.75 (0.5, 1) mcg of calcitriol. The mean eGFR at baseline was 97.4 mL/min/1.73 m^2 and 45%, 10% and 0% had mild, moderate and severe renal impairment, respectively, at baseline. During the trial, most patients received 100 mcg and the dose range was 50 to 100 mcg administered subcutaneously once daily in the thigh.

Table 2 lists common adverse reactions associated with NATPARA use in the clinical trial. Common adverse reactions were reactions that occurred in ≥5% of subjects and occurred more commonly on NATPARA than on placebo.

Table 2: Common Adverse Reactions associated with NATPARA use in Subjects with Hypoparathyroidism
Adverse Reaction | Placebo (N=40) % | NATPARA (N=84) %
Paresthesia | 25 | 31
Hypocalcemia [Hypocalcemia combines reported events of hypocalcemia and blood calcium decreased; hypercalciuria combines reported events of hypercalciuria and urine calcium increased; and hypercalcemia combines reported events of hypercalcemia and blood calcium increased.] | 23 | 27
Headache | 23 | 25
Hypercalcemia | 3 | 19
Nausea | 18 | 18
Hypoesthesia | 10 | 14
Diarrhea | 3 | 12
Vomiting | 0 | 12
Arthralgia | 10 | 11
Hypercalciuria | 8 | 11
Pain in extremity | 8 | 10
Upper respiratory tract infection | 5 | 8
Abdominal pain upper | 3 | 7
Sinusitis | 5 | 7
Blood 25-hydroxycholecalciferol decreased | 3 | 6
Hypertension | 5 | 6
Hypoesthesia facial | 3 | 6
Neck pain | 3 | 6

Hypercalcemia

In the overall pivotal trial, a greater proportion of patients on NATPARA had albumin-corrected serum calcium above the normal range (8.4 to 10.6 mg/dL). During the entire trial duration 3 patients on NATPARA and 1 patient on placebo had a calcium level above 12 mg/dL. Table 3 displays the number of subjects who had albumin-corrected serum calcium levels above the normal range (8.4 to 10.6 mg/dL) by study treatment period in the placebo-controlled study based on routine monitoring at each trial visit. More patients randomized to NATPARA had hypercalcemia in both phases of the study (note: all trial participants underwent a 50% reduction in active vitamin D dose at randomization).

Table 3: Proportion of Subjects with Albumin-Corrected Serum Calcium Greater Than Upper Limit of Normal (10.6 mg/dL) During the Treatment Period
 | Titration Period (Weeks 0-12) [NATPARA was only titrated upwards for up to Week 6] |  | Maintenance Period (Weeks 12-24)
Albumin-corrected serum calcium | Placebo N=40 | NATPARA N=84 | Placebo N=40 | NATPARA N=84
>10.6 to ≤12 mg/dL | 0% | 30% | 0% | 10%
>12 to ≤13 mg/dL | 0% | 2% | 3% | 0%

Hypocalcemia

Table 4 displays the number of subjects who had albumin-corrected serum calcium levels below 8.4 mg/dL by treatment period in the placebo-controlled study based on routine monitoring at each trial visit. More patients randomized to placebo had hypocalcemia of less than 7 mg/dL in the titration phase (note: all trial participants underwent a 50% reduction in active vitamin D dose at randomization). More patients randomized to NATPARA had hypocalcemia of less than 7 mg/dL in the dose maintenance phase.

Table 4: Proportion of Subjects with Albumin-Corrected Serum Calcium Below the Lower Limit of Normal (8.4 mg/dL) During the Treatment Period
 | Titration Period (Weeks 0-12) |  | Maintenance Period (Weeks 12-24)
Albumin-corrected serum calcium | Placebo N=40 | NATPARA N=84 | Placebo N=40 | NATPARA N=84
≥7 to <8.4 mg/dL | 98% | 79% | 75% | 71%
<7 mg/dL | 18% | 6% | 0% | 12%

The risk of hypocalcemia increases when NATPARA is withdrawn. At the end of the trial, NATPARA and placebo were withdrawn, calcium and active vitamin D were returned to baseline doses and subjects were followed for 4 weeks. During this withdrawal phase, more patients previously randomized to NATPARA experienced an albumin-corrected serum calcium value of less than 7 mg/dL (5.0% versus 17% for previous treatment with placebo and NATPARA, respectively). Twenty subjects (24%) previously randomized to NATPARA experienced adverse reactions of hypocalcemia in the post-treatment phase compared to three subjects (8%) previously randomized to placebo. Five subjects previously randomized to NATPARA with albumin-corrected serum calcium below 7 mg/dL required treatment with IV calcium gluconate to correct hypocalcemia.

Hypercalciuria

Treatment with NATPARA did not lower 24-hour urinary calcium excretion in the placebo-controlled trial. The proportion of subjects with hypercalciuria (defined as urine calcium levels of >300 mg/24 hours) was similar at baseline and trial end in the NATPARA and placebo groups. The median (IQR) 24-hour Urine Calcium at trial end was similar between NATPARA [231 (168-351) mg/24 hours], and placebo [232 (139-342) mg/24 hours]. At trial end, serum calcium values between NATPARA and placebo were also similar. Risk of hypercalciuria throughout the trial was related to serum calcium levels. To minimize the risk of hypercalciuria, NATPARA should be dosed to a target albumin-corrected total serum calcium within the lower half of the normal range (i.e., between 8 and 9 mg/dL) [see Dosage and Administration (2.1)].

6.2 Immunogenicity

NATPARA may trigger the development of antibodies. In the placebo-controlled study in adults with hypoparathyroidism, the incidence of anti-PTH antibodies was 8.6% (3/35) and 5.9% (1/17) in subjects who received subcutaneous administration of 50 to 100 mcg NATPARA or placebo once daily for 24 weeks, respectively.

Across all clinical studies in subjects with hypoparathyroidism following treatment with NATPARA for up to 2.6 years, the immunogenicity incidence rate was 16.1% (14/87). These 14 subjects had low titer anti-PTH antibodies and, of these, 3 subjects subsequently became antibody negative. One of these subjects had antibodies with neutralizing activity; this subject maintained a clinical response with no evidence of immune-related adverse reactions. Anti-PTH antibodies did not appear to affect efficacy or safety during the clinical trials but their longer-term impact is unknown.

Immunogenicity assay results are highly dependent on the sensitivity and specificity of the assay and may be influenced by several factors such as: assay methodology, sample handling, timing of sample collection, concomitant medication, and underlying diseases. For these reasons, comparison of the incidence of antibodies to NATPARA with the incidence of antibodies to other products may be misleading.

6.3 Postmarketing Experience

The following adverse reactions have been identified during post-approval use of NATPARA. Because these reactions are reported voluntarily from a population of uncertain size, it is not always possible to reliably estimate their frequency or establish a causal relationship to drug exposure.

- Hypersensitivity reactions (e.g., anaphylaxis, dyspnea, angioedema, urticaria, and rash).
- Seizures due to hypocalcemia

7 DRUG INTERACTIONS

7.1 Alendronate

Co-administration of alendronate and NATPARA leads to reduction in the calcium-sparing effect, which can interfere with the normalization of serum calcium. Concomitant use of NATPARA with alendronate is not recommended.

7.2 Digoxin

NATPARA causes transient increase in calcium and therefore, concomitant use of NATPARA and cardiac glycosides (e.g., digoxin) may predispose patients to digitalis toxicity if hypercalcemia develops. Digoxin efficacy is reduced if hypocalcemia is present. In patients using NATPARA concomitantly with digoxin, carefully monitor serum calcium and digoxin levels, and patients for signs and symptoms of digoxin toxicity. Adjustment of digoxin and/or NATPARA may be needed. No drug-drug interaction study has been conducted with digoxin and NATPARA.

8 USE IN SPECIFIC POPULATIONS

8.1 Pregnancy

Risk Summary

Available data with NATPARA Injection use in pregnant women are insufficient to inform a drug associated risk of birth defects, miscarriage or adverse maternal or fetal outcomes. There are disease associated risks to the mother and the fetus related to hypocalcemia in pregnancy. (see Clinical Considerations). In animal reproduction studies, no adverse developmental effects were observed when pregnant rats and rabbits were administered parathyroid hormone subcutaneously during the period of organogenesis at doses resulting in 123 times and 8 times, respectively, the human exposure at the 100 mcg/day clinical dose. When female rats were administered parathyroid hormone subcutaneously prior to birth and continuing to weaning at doses resulting in 10 times the human exposure at the 100 mcg/day clinical dose, increased incidence of dehydration, broken palate and palate injuries related to incisor misalignment and mortality were observed in offspring (see Data).

All pregnancies have a background risk of major birth defects, loss, and other adverse outcomes.In the U.S. general population, the estimated major birth defects and miscarriage in clinically recognized pregnancies is 2 to 4% and 15 to 20%, respectively.

Clinical Considerations

Disease-Associated Maternal and Embryo/Fetal Risk

Maternal hypocalcemia can result in an increased rate of spontaneous abortion, premature and dysfunctional labor, and possibly preeclampsia.

Fetal/Neonatal adverse reactions

Infants born to mothers with hypocalcemia can have associated fetal and neonatal hyperparathyroidism, which in turn can cause fetal and neonatal skeletal demineralization, subperiosteal bone resorption, osteitis fibrosa cystica and neonatal seizures. Infants born to mothers with hypocalcemia should be carefully monitored for signs of hypocalcemia or hypercalcemia, including neuromuscular irritability (ranging from myotonic jerks to seizures), apnea, cyanosis and cardiac rhythm disorders.

Data

Animal Data

In pregnant rats given subcutaneous doses up to 1000 mcg/kg/day during organogenesis there were no findings observed at 123 times the 100 mcg/day clinical dose based on AUC. In pregnant rabbits given subcutaneous doses of 5, 10 and 50 mcg/kg/day during organogenesis, various skeletal alterations including incomplete ossification in <35% of litters given 10 mcg/kg/day which were statistically significant but within historical control range at exposures 8 times the 100 mcg/kg/day clinical dose. There was a fetus with spina bifida in the 50 mcg/kg/day dose group at 72 times the 100 mcg/day clinical dose based on AUC. Given the association of folic acid deficiency and neural tube defects this finding may be related to decreased body weight and food consumption in the pregnant rabbits.

Developmental effects were observed in a peri /postnatal study in pregnant rats given subcutaneous doses of 100, 300, 1000 mcg/kg/day from organogenesis through lactation while an entire litter was stillborn in the 300 mcg/kg/day group (34 times the 100 mcg/day clinical dose based on AUC) and an entire litter from the 1000 mcg/kg/day (123 times the 100 mcg/day clinical dose based on AUC) was dead by postnatal day 4. Increased incidence of morbidity associated with dehydration, broken palate and palate injuries related to incisor misalignment and mortality were found in pups from litters given 100 mcg/kg/day (10 times the 100 mcg/day clinical dose based on AUC). At 300 mcg/kg/day there was a litter with kidney dilatation and another with an extra liver lobe. There was a single pup with a diaphragmatic hernia from a litter exposed to 1000 mcg/kg/day.

8.2 Lactation

Risk Summary

There are no data available on the presence of parathyroid hormone in the breast milk, the effects on the breastfed infant or the effects on milk production. Parathyroid hormone is present in the milk of lactating rats (see Data). When a drug is present in animal milk, it is likely that the drug will be present in human milk. The developmental and health benefits of breastfeeding should be considered along with the mother's clinical need for NATPARA and any potential adverse effects on the breastfed child from NATPARA or from the underlying maternal condition.

Clinical Considerations

Infants exposed to parathyroid hormone through breast milk should be monitored for signs and symptoms of hypercalcemia or hypocalcemia. Monitoring of serum calcium in the infant should be considered.

Data

Animal Data

In a lactation transfer study where rats were given subcutaneous doses of 300 and 1000 mcg/kg/day from day 17 of gestation through day 16 of lactation, mean parathyroid hormone concentration in milk was approximately 10 ng/mL at the dose of 1000 mcg/kg/day, 42 times lower in milk than in plasma. The concentration of drug in animal milk does not necessarily predict the concentration of drug in human milk.

8.4 Pediatric Use

Safety and efficacy in patients less than 18 years of age has not been established. Avoid use of NATPARA in patients who are at increased baseline risk for osteosarcoma including pediatric and young adult patients with open epiphyses [see Boxed Warning, Warnings and Precautions (5.1)].

8.5 Geriatric Use

Clinical studies of NATPARA did not include sufficient numbers of subjects aged 65 and over to determine whether response in these subjects is different from younger subjects. In general, dose selection for elderly individuals should be cautious, usually starting at the low end of the dosing range, reflecting the greater frequency of decreased hepatic, renal, or cardiac function, and of concomitant disease or other drug therapy [see Clinical Pharmacology (12.3)].

8.6 Renal Impairment

Clinical studies of NATPARA did not include sufficient numbers of subjects with moderate and severe renal impairment to determine whether they respond differently from subjects with mild renal impairment or normal renal function. Some of the mechanisms of action of NATPARA (e.g., conversion of 25-OH vitamin D to 1,25-OH2 vitamin D) are dependent on renal function. NATPARA is eliminated by the kidney and maximum drug levels increased with renal impairment [see Clinical Pharmacology (12.3)].

10 OVERDOSAGE

Accidental overdose in studies in hypoparathyroidism occurred in 1 subject who received a 150 mcg dose and experienced mild palpitations. Serum calcium 24 hours later was 10.3 mg/dL. In the event of overdose, the patient should be carefully monitored for hypercalcemia by a medical professional [see Adverse Reactions (6.1)].

11 DESCRIPTION

The active ingredient in NATPARA, parathyroid hormone, is produced by recombinant DNA technology using a modified strain of Escherichia coli. Parathyroid hormone has 84 amino acids and a molecular weight of 9425 daltons; the amino acid sequence for parathyroid hormone is shown below in Figure 1.

Figure 1: Amino Acid Sequence of Parathyroid Hormone

NATPARA (parathyroid hormone) for injection for subcutaneous use is supplied as a medication cartridge, which is comprised of a multiple-dose, dual-chamber glass cartridge containing a sterile lyophilized powder and a sterile diluent, within a plastic cartridge holder. The sterile lyophilized powder contains either 0.4 mg or 0.8 mg or 1.21 mg or 1.61 mg of parathyroid hormone, depending on dosage strength, and 4.5 mg sodium chloride, 30 mg mannitol, and 1.26 mg citric acid monohydrate. The volume of the sterile diluent is 1.13 mL and the diluent contains a 3.2 mg/mL aqueous solution of m-cresol.

The disposable NATPARA medication cartridge is designed for use with a reusable mixing device for product reconstitution and a reusable Q-Cliq pen for drug delivery. The Q-Cliq pen delivers a fixed volumetric dose of 71.4 µL. Using the Q-Cliq pen, each NATPARA dual chamber cartridge delivers 14 doses of NATPARA [see Dosage Forms and Strengths (3)].

12 CLINICAL PHARMACOLOGY

12.1 Mechanism of Action

NATPARA is a parathyroid hormone. Parathyroid hormone raises serum calcium by increasing renal tubular calcium reabsorption, increasing intestinal calcium absorption (i.e., by converting 25-OH vitamin D to 1,25-OH2 vitamin D) and by increasing bone turnover which releases calcium into the circulation.

12.2 Pharmacodynamics

The pharmacodynamics in subjects with hypoparathyroidism after single subcutaneous administration of 50 and 100 mcg dose of NATPARA in the thigh were evaluated.

Treatment with NATPARA increases serum calcium levels (Figure 2). The increase in serum calcium levels in hypoparathyroidism subjects occurs in a dose-related manner. Mean peak serum calcium levels are reached between 10 and 12 hours following a single subcutaneous injection and the increase in serum calcium above baseline is sustained for more than 24 hours after administration. The maximum mean increases of serum calcium, which occurred at 12 hours, were approximately 0.5 mg/dL and 0.7 mg/dL from baseline with the 50 mcg and 100 mcg doses, respectively. The mean calcium intake for the 50 and 100 mcg doses was 1700 mg [see Clinical Pharmacology (12.3)].

12.3 Pharmacokinetics

Following single subcutaneous(SC) injections of NATPARA at 50 mcg and 100 mcg in subjects with hypoparathyroidism, peak plasma concentrations (mean Tmax) of NATPARA occurs within 5 to 30 minutes and a second usually smaller peak at 1 to 2 hours. The plasma AUC increased in a dose-proportional manner from 50 mcg to 100 mcg. The apparent terminal half-life (t1/2) was 3.02 and 2.83 hours for the 50 and 100 mcg dose, respectively.

Mean unadjusted concentration-time profiles of parathyroid hormone in plasma following SC administration of 100 mcg of NATPARA are presented in Figure 2. One 100 mcg dose of NATPARA provides a 24-hour calcemic response in hypoparathyroidism subjects.

Figure 2 Mean (±SE) Unadjusted Plasma Parathyroid Hormone and Albumin-Corrected Serum Calcium Concentration Following 100 mcg SC Administration in Subjects with Hypoparathyroidism

Absorption:

NATPARA administered subcutaneously has an absolute bioavailability of 53%.

Distribution:

NATPARA has a volume of distribution of 5.35 L at steady state.

Metabolism:

In vitro and in vivo studies demonstrated that the clearance of parathyroid hormone is primarily a hepatic process with a lesser role played by the kidneys.

Excretion:

In the liver, most of the intact parathyroid hormone is cleaved by cathepsins. In the kidney, a small amount of parathyroid hormone binds to physiologic PTH-1 receptors, but most is filtered at the glomerulus. C-terminal fragments are also cleared efficiently by glomerular filtration.

Hepatic Impairment:

A pharmacokinetic study was conducted in 6 men and 6 women with moderate hepatic impairment (Child-Pugh Classification of 7-9 [Grade B]) as compared with a matched group of 12 subjects with normal hepatic function. Following a single 100-mcg subcutaneous dose, the mean Cmax and baseline-corrected Cmax values were 18% to 20% greater in the moderately impaired subjects than in those with normal function. There were no apparent differences in the serum total calcium concentration-time profiles between the 2 hepatic function groups. No dose adjustment for NATPARA is recommended in patients with mild to moderate hepatic impairment.

Renal Impairment:

Pharmacokinetics following a single NATPARA 100 mcg subcutaneous dose was evaluated in 16 subjects with normal renal function (creatinine clearance (CLcr) >90 mL/min) and 16 subjects with renal impairment. The mean maximum concentration (Cmax) of parathyroid hormone following administration of 100 mcg NATPARA in subjects with mild (CLcr 60 to 90 mL/min) and moderate (CLcr 30 to 60 mL/min) renal impairment was approximately 22% higher than that observed in subjects with normal renal function. Exposure to parathyroid hormone as measured by AUC0-last and baseline-corrected AUC0-last was approximately 3.9% and 2.5%, respectively, higher than that observed for subjects with normal renal function. No studies were conducted in patients with severe renal impairment or in renal impairment patients on dialysis.

Age, Sex, Race, and Weight:

Based on population pharmacokinetic analysis, age, sex, race, and body weight did not significantly affect the NATPARA pharmacokinetics.

13 NONCLINICAL TOXICOLOGY

13.1 Carcinogenesis, Mutagenesis, Impairment of Fertility

In a 104-week carcinogenicity study in rats, parathyroid hormone was given subcutaneously at doses of 10, 50 and 150 mcg/kg/day. These doses resulted in systemic exposures that were, respectively 3 to 71 times higher than systemic exposure observed in humans following a subcutaneous dose of 100 mcg/day based on AUC. Systemic exposure at the 10 mcg/kg/day dose of parathyroid hormone was 3-5 times greater AUC than the exposure observed in hypoparathyroidism subjects at the clinical dose of 100 mcg/day. This is the lowest dose at which a parathyroid hormone-related increase in bone tumors was observed in rats. Higher exposures resulted in a marked dose-related increase in all bone tumors including osteoma, osteoblastoma and osteosarcomas in both sexes. The bone tumors in rats occurred in association with a large increase in bone mass and focal osteoblast hyperplasia. However, since bone metabolism in the rat differs from that in humans, the relevance of these animal findings to humans is uncertain.

Parathyroid hormone is not genotoxic in any of the following test systems: the bacterial reverse mutation (Ames) assay or the in vitro mammalian cell forward-gene mutation (AS52/XPRT) assay study with and without metabolic activation.

No effect on fertility was observed in male and female rats given parathyroid hormone at doses up to 1000 mcg/kg/day (120 times systemic exposure after a clinical dose of 100 mcg/day).

13.2 Animal Toxicology and/or Pharmacology

In pregnant rats given subcutaneous doses up to 1000 mcg/kg/day during organogenesis there were no findings observed at 123 times the 100 mcg/day clinical dose based on AUC. In pregnant rabbits given subcutaneous doses of 5, 10 and 50 mcg/kg/day during organogenesis, various skeletal alterations including in complete ossification in <35% of litters given 10 mcg/kg/day which were statistically significant but within historical control range at exposures 8 times the 100 mcg/kg/day clinical dose. There was a fetus with spina bifida in the 50 mcg/kg/day dose group at 72 times the 100 mcg/day clinical dose based on AUC. Given the association of folic acid deficiency and neural tube defects this finding may be related to decreased body weight and food consumption in the pregnant rabbits.

Developmental effects were observed in a peri-/post-natal study in pregnant rats given subcutaneous doses of 100, 300, 1000 mcg/kg/day from organogenesis through lactation while an entire litter was stillborn in the 300 mcg/kg/day group (34 times the 100 mcg/day clinical dose based on AUC) and an entire litter from the 1000 mcg/kg/day (123 times the 100 mcg/day clinical dose based on AUC) was dead by postnatal day 4. Increased incidence of morbidity associated with dehydration, broken palate and palate injuries related to incisor misalignment and mortality were found in pups from litters given 100 mcg/kg/day (10 times the 100 mcg/day clinical dose based on AUC). At 300 mcg/kg/day there was a litter with kidney dilatation and another with an extra liver lobe. There was a single pup with a diaphragmatic hernia from a litter exposed to 1000 mcg/kg/day.

14 CLINICAL STUDIES

Study in Patients with Established Hypoparathyroidism

The efficacy of NATPARA was evaluated in a 24-week, randomized, double-blind, placebo-controlled, multicenter trial. In this trial, patients with established hypoparathyroidism receiving calcium and active forms of vitamin D (vitamin D metabolite or analogs) were randomized (2:1) to NATPARA (n=84) or placebo (n=40). The mean age was 47 years (range, 19 to 74 years), 79.0% were females and 96.0% were Caucasian, 0.8% were Black, and 1.6% were Asian. Patients had hypoparathyroidism for on average 15 years and hypoparathyroidism was caused by post-surgical complications in 71% of cases, idiopathic hypoparathyroidism in 25%, DiGeorge Syndrome in 3%, and auto-immune hypoparathyroidism in 1%. Patients with hypoparathyroidism due to calcium-sensing receptor mutations were excluded from the trial. The mean eGFR at baseline was 97.4 mL/min/1.73 m^2 and 45%, 10% and 0% had mild, moderate and severe renal impairment, respectively, at baseline.

Before randomization, participants entered a 2-16 weeks run-in phase. In this phase calcium supplement and active vitamin D doses were adjusted to target an albumin-corrected serum calcium concentration between 8.0 and 9.0 mg/dL and 25-hydroxyvitamin D was replaced in patients with insufficient stores. At randomization, baseline serum calcium was 8.6 mg and participants were receiving a median (interquartile range) daily oral calcium dose of 2000 (1250, 3000) mg and a median daily oral active vitamin D dose equivalent to 0.75 mcg (0.5, 1) of calcitriol.

At randomization, active forms of vitamin D were reduced by 50% and patients were randomized to NATPARA 50 mcg daily or placebo. Randomization was followed by a 12-week NATPARA titration phase and a 12-week NATPARA dose maintenance phase. During the titration phase NATPARA was increased by 25 mcg increments every four weeks up to a maximum of 100 mcg. Titration was indicated for patients who could not achieve independence from active vitamin D and who could not reduce oral calcium to 500 mg or less per day. At end of treatment, 56% of subjects randomized to NATPARA were receiving 100 mcg of NATPARA per day, 26% were receiving 75 mcg of NATPARA per day, and 18% were receiving 50 mcg of NATPARA per day. Doses of co-administered active forms of vitamin D and calcium were adjusted (reduced or increased) to maintain albumin-corrected serum calcium within a desired target range throughout the trial in both arms.

For the efficacy analysis, subjects that fulfilled three components of a three-part response criterion were considered responders. A responder was defined as an individual who had: at least a 50% reduction from baseline in the dose of active vitamin D, at least a 50% reduction from baseline in the dose of oral calcium supplementation and an albumin-corrected total serum calcium concentration between 7.5 mg/dL and 10.6 mg/dL.

At the end of treatment, significantly (p-value <0.001) more subjects treated with NATPARA [46/84 (54.8%)] compared to placebo [1/40 (2.5%)] met the response criterion. Forty-two percent (35/84) of subjects randomized to NATPARA were independent of active forms of vitamin D and were on no more than 500 mg of oral calcium, compared with 2.5% (1/40) of subjects randomized to placebo (p<0.001). There were no differences in the proportion of patients with a calcium level between 7.5 mg and 10.6 mg at end of treatment between subjects randomized to NATPARA and placebo.

Table 5 shows the proportion of individuals who, at the end of treatment, fulfilled the 3-part response criterion. Table 6 provides results on individual components of the response criterion.

Table 5: Proportion of Responders [Response = at least a 50% reduction from baseline in the dose of active vitamin D + at least a 50% reduction from baseline in the dose of oral calcium supplementation + an albumin-corrected total serum calcium concentration between 7.5 mg/dL and 10.6 mg/dL] at End of Treatment – Intent to Treat Population
 | Placebo (N=40) | NATPARA (N=84)
Efficacy Endpoint
Responder at End of Treatment, based on investigator-prescribed data - n (%) | 1 (2.5) | 46 (54.8) (p <0.001) [Based on Fisher's exact test]

Table 6: Proportion of Patients with Calcium and Active Vitamin D Dose Reduction and Albumin-Corrected Serum Calcium between 7.5 and 10.6 mg/dL at End of Treatment – ITT Population
Components of the Efficacy Endpoint
 |  | Placebo (N=40) | NATPARA (N=84)
Oral Calcium | Reduction ≥50% - n (%) | 3 (7.5) | 58 (69.0)
Oral Calcium | Percent Change from Baseline - Mean (SD) [Based on Analysis of Covariance (ANCOVA) model with percent change as the dependent variable and the treatment as the factor and baseline calcium dose as the covariate.] | 6.5 (38.5) | -51.8 (44.6) (p <0.001)
Oral Active Vitamin D | Reduction ≥50% - n (%) | 18 (45.0) | 73 (86.9)
ACSC maintained between ≥7.5 mg/dL to ≤ULN - n (%) |  | 35 (87.5) | 73 (86.9)
ACSC = albumin-corrected total serum calcium; EOT = end of treatment; N = total number of subjects; n = number of subjects meeting the specified endpoint; SD = standard deviation; ULN = upper limit of normal

16 HOW SUPPLIED/STORAGE AND HANDLING

16.1 How Supplied

NATPARA (parathyroid hormone) for injection for subcutaneous use is supplied as a medication cartridge, which is comprised of a multiple-dose, dual-chamber glass cartridge containing a sterile lyophilized powder and a sterile diluent, within a plastic cartridge holder. The medication cartridge is available in 4 dosage strengths (25, 50, 75, and 100 mcg/dose). The 25 mcg/dose cartridge contains 0.4 mg parathyroid hormone; the 50 mcg/dose cartridge contains 0.8 mg parathyroid hormone; the 75 mcg/dose cartridge contains 1.21 mg parathyroid hormone; the 100 mcg/dose cartridge contains 1.61 mg parathyroid hormone.

NATPARA is supplied in the following packages:

  - 2 cartridges of 25 mcg/dose strength (NDC 68875-0202-2)
  - 2 cartridges of 50 mcg/dose strength (NDC 68875-0203-2)
  - 2 cartridges of 75 mcg/dose strength (NDC 68875-0204-2)
  - 2 cartridges of 100 mcg/dose strength (NDC 68875-0205-2)

The disposable NATPARA medication cartridge is designed for use with a reusable mixing device for product reconstitution and a reusable Q-Cliq pen injector for drug delivery. The Q-Cliq pen is designed to deliver a fixed volumetric dose of 71.4 µL. Using the Q-Cliq pen, each NATPARA medication cartridge delivers 14 doses; each dose contains 25, 50, 75, or 100 mcg of NATPARA depending on the product dosage strength.

Designed for use with 31G × 8 mm BD Ultra-Fine™ Pen Needles.

The mixing device, provided in a separate carton, is designed to enable reconstitution of the product before the first use of each cartridge. The mixing device can be used to reconstitute up to 6 NATPARA medication cartridges.

The Q-Cliq pen, packaged in a separate carton, can be used for up to 2 years of daily treatment by replacing the reconstituted cartridge every two weeks (14 days).

Instructions for use of the mixing device and the Q-Cliq pen are provided with the NATPARA medication cartridges.

16.2 Storage and Handling

Prior to reconstitution, the dual-chamber NATPARA medication cartridge should be stored in the package provided at refrigerated temperature, 36 to 46°F (2 to 8°C). After reconstitution, the medication cartridge should be stored in the Q-Cliq pen under refrigeration at 36 to 46°F (2 to 8°C). The reconstituted product can be used for up to 14 days under these conditions. Store away from heat and light. Avoid exposure to elevated temperatures. Discard reconstituted NATPARA medication cartridges after 14 days.

Do not freeze or shake. Do not use NATPARA if it has been frozen or shaken.

The mixing device and empty Q-Cliq pen can be stored at room temperature.

Safely discard needles.

17 PATIENT COUNSELING INFORMATION

Advise the patient to read the FDA-approved patient labeling (Medication Guide and Instructions for Use).

General Counseling Information – Prior to treatment, patients should fully understand the risks and benefits of NATPARA. Ensure that all patients receive the Medication Guide and Instructions for Use document prior to initiating NATPARA therapy.

Potential Risk of Osteosarcoma

[see Warnings and Precautions (5.1)]

Advise patients that the active ingredient in NATPARA, parathyroid hormone, caused an increase in the incidence of osteosarcoma (a malignant bone tumor) in male and female rats in dedicated lifelong carcinogenicity studies and that the risk of osteosarcoma in rats was dependent on parathyroid hormone dose administered, on treatment duration and occurred at exposure levels close to the clinical exposure range. Based on these findings NATPARA may carry a potential risk to humans.

Patients should be advised that because of a potential risk of osteosarcoma, NATPARA is only recommended for patients who cannot be well-controlled on oral calcium supplementation and on active forms of vitamin D. In addition, use of NATPARA should be avoided in patients who have risk factors for osteosarcoma unless the benefits of using NATPARA in these patients are determined to outweigh this potential risk.

Instruct patients to promptly report signs and symptoms of possible osteosarcoma such as persistent localized pain or occurrence of a new soft tissue mass that is tender to palpation.

NATPARA REMS

[see Warnings and Precautions (5.1, 5.2)]

- NATPARA is available only through a restricted program called the NATPARA REMS Program, because of the potential risk of osteosarcoma.
- Counsel patients on the benefits and risks of NATPARA using the NATPARA Patient Brochure.
- Patients must sign the NATPARA REMS Patient-Prescriber Acknowledgment Form.
- Provide patient with a copy of the NATPARA Patient Brochure and NATPARA REMS Patient-Prescriber Acknowledgment Form.
- NATPARA is only available through certified pharmacies, provide information to your patients about how they will receive prescriptions:
  - Submit the NATPARA prescription to the NATPARA REMS Program Coordinating Center (by fax or email).
  - The REMS Program Coordinating Center will send the prescription to a certified pharmacy to fill after verifying that the prescriber is certified and a Patient-Prescriber Acknowledgment Form is on record.
  - The REMS Program Coordinating Center will call the patient and provide the name and phone number of the certified pharmacy that will be dispensing NATPARA.
  - The certified pharmacy will contact the patient to arrange the date to ship NATPARA once the prescription is filled.

Severe Hypercalcemia

[see Warnings and Precautions (5.3)]

Instruct patients that severe hypercalcemia can occur when starting or adjusting NATPARA dose and/or when making changes to co-administered drugs known to raise serum calcium. Instruct patients to: report symptoms of hypercalcemia promptly, report any changes to co-administered drug(s) known to influence calcium levels and follow recommended serum calcium monitoring.

Severe Hypocalcemia

[see Warnings and Precautions (5.4)]

Instruct patients that severe hypocalcemia can occur if NATPARA dosing is abruptly interrupted or discontinued. Instruct patients to report symptoms of hypocalcemia promptly, report interruption in NATPARA dosing and follow recommended serum calcium monitoring. In the event of NATPARA dose interruption, patients should contact their healthcare provider, as their doses of active vitamin D and calcium supplementation may need adjustment.

Digoxin Toxicity

[see Warnings and Precautions (5.5)]

Instruct patients to report use of digoxin containing medication, and follow recommended serum calcium monitoring.

Hypersensitivity

[see Warnings and Precautions (5.6)]

Instruct patients that serious hypersensitivity reactions (anaphylaxis, dyspnea, angioedema, urticaria, rash) can occur with NATPARA. Instruct patients to immediately report symptoms of serious hypersensitivity reactions and to seek medical attention if a reaction occurs.

Lactation

Advise women that infants exposed to parathyroid hormone through breast milk should be monitored for symptoms of hypercalcemia or hypocalcemia.

Dosing Instructions

Instruct patients to read the Instructions for Use document carefully. The patient or caregiver should be instructed by a physician or an appropriately qualified healthcare professional in the proper technique for administering subcutaneous injections using the mixing device and the Q-Cliq pen, including the use of aseptic technique. The patient and caregiver should be cautioned that needles must not be re-used and instructed in safe disposal procedures. A puncture-resistant container for disposal of used needles should be supplied to the patient along with instructions for safe disposal of the full container. Instruct patients to never share their devices with other patients. Advise patients to never transfer the contents of the delivery device to a syringe.

After reconstitution, each NATPARA medication cartridge can be used for 14 subcutaneous injections. After the use period, only the cartridge should be discarded. The Q-Cliq pen can be used for up to 2 years by replacing the reconstituted medication cartridge every two weeks (14 days).

Common Adverse Reactions

[see Adverse Reactions (6.1)]

Inform patients that the most common adverse reactions occurring in patients on NATPARA were paresthesia, hypocalcemia, headache, hypercalcemia, nausea, hypoaesthesia, diarrhea, vomiting, arthralgia, hypercalciuria and pain in extremity.

Manufactured by:
Takeda Pharmaceuticals U.S.A., Inc.
Cambridge, MA 02142 USA

U.S. License Number 1898

For information about NATPARA contact:
Takeda Pharmaceuticals U.S.A., Inc.
Cambridge, MA 02142
USA
1-800-828-2088
www.NATPARA.com

NATPARA is a registered trademark of Takeda Pharmaceuticals U.S.A., Inc.

Q-CLIQ is a registered trademark of Takeda Pharmaceuticals U.S.A., Inc.

Ultra-Fine™ is a trademark of Becton, Dickinson and company.

©2025 Takeda Pharmaceuticals U.S.A., Inc. All rights reserved.

Medication Guide

NATPARA® (nat-PAH-rah)
(parathyroid hormone)
for injection

What is the most important information I should know about NATPARA?

- possible bone cancer (osteosarcoma). During animal drug testing, NATPARA caused some rats to develop a bone cancer called osteosarcoma. It is not known if people who take NATPARA will have a higher chance of getting osteosarcoma. Tell your healthcare provider right away if you have pain in any areas of your body that does not go away, or any new or unusual lumps or swelling under your skin that is tender to touch. These are some of the signs and symptoms of osteosarcoma and your healthcare provider may need to do further tests.
  - NATPARA is only available through the NATPARA Risk Evaluation and Mitigation Strategy (REMS) Program. The purpose of the NATPARA REMS program is to inform patients about the potential risk of osteosarcoma associated with the use of NATPARA. For more information about this REMS program, call 1-855-NATPARA (1-855-628-7272) or go to www.NATPARAREMS.com.

NATPARA may cause serious side effects, including:

- high blood calcium (hypercalcemia). NATPARA can cause some people to have a higher blood calcium level than normal. Your healthcare provider should check your blood calcium before you start and during your treatment with NATPARA. Tell your healthcare provider if you have nausea, vomiting, constipation, low energy, or muscle weakness. These may be signs that you have too much calcium in your blood.
- low blood calcium (hypocalcemia). People who stop using or miss a dose of NATPARA may have an increased risk of severe low blood calcium levels. Tell your healthcare provider if you have tingling of your lips, tongue, fingers and feet, twitching of face muscles, cramping of feet and hands, seizures, depression, or have problems thinking or remembering.

Tell your healthcare provider right away if you have any of these signs and symptoms of high or low blood calcium levels.

What is NATPARA?

- NATPARA is a prescription parathyroid hormone (PTH) used with calcium and vitamin D to control low blood calcium (hypocalcemia) in people with low PTH blood levels (hypoparathyroidism).
- NATPARA is only for people who do not respond well to treatment with calcium and active forms of vitamin D alone, because it may increase the possible risk of bone cancer (osteosarcoma).
- NATPARA was not studied in people with hypoparathyroidism caused by calcium-sensing receptor mutations.
- NATPARA was not studied in people who get sudden hypoparathyroidism after surgery.

It is not known if NATPARA is safe and effective for children 18 years of age and younger.

NATPARA should not be used in children and young adults whose bones are still growing.

Do not use NATPARA if you are allergic to parathyroid hormone or any of the ingredients in NATPARA. See the end of this Medication Guide for a complete list of ingredients in NATPARA.

Before you start using NATPARA, tell your healthcare provider about all of your medical conditions, including if you:

- have Paget's disease or other bone disease
- have or have had cancer in your bones
- have or have had radiation therapy
- have or had too much calcium in your blood
- have high blood levels of certain electrolytes (alkaline phosphatase)
- are pregnant or plan to become pregnant. It is not known if NATPARA will harm your unborn baby.
- are breastfeeding or plan to breastfeed. It is not known if NATPARA passes into your breast milk. You and your healthcare provider should decide if you will use NATPARA or breastfeed. You should not do both.

Tell your healthcare provider about all the medicines you take, including prescription and over-the-counter medicines, vitamins, and herbal supplements.

NATPARA and other medicines may affect each other causing side effects.

Especially tell your healthcare provider if you are taking medicines that contain digoxin, alendronate, calcium supplements or food products that contain calcium, or active vitamin D.

Know the medicines you take. Keep a list of them to show your healthcare provider or pharmacist each time you get a new medicine.

How should I use NATPARA?

- Read the detailed Instructions for Use at the end of this Medication Guide.
- Use NATPARA exactly as your healthcare provider tells you to.
- NATPARA is given with the Q-Cliq® pen injector. Before you use NATPARA for the first time, a healthcare provider will show you how to use the Q-Cliq pen the right way and how to properly mix NATPARA using the mixing device.
- Do not stop taking or change your dose of NATPARA unless your healthcare provider tells you to. Your calcium level could become dangerously low.
- Give NATPARA 1 time each day in your thigh just under your skin (subcutaneous).
- After you mix NATPARA, each medicine cartridge can be used for 14 injections (14 doses). After you use the 14 doses throw away the cartridge.
- Do not throw away the Q-Cliq pen. It can be re-used for up to 2 years, by changing the mixed NATPARA medicine cartridges every 2 weeks (14 days).
- Look at NATPARA for any discoloration or particles in the medicine. It should be colorless. It is normal to see small particles in the liquid.
- Do not transfer the medicine from the NATPARA medicine cartridge to a syringe. This can cause you to use the wrong dose of NATPARA.
- Your healthcare provider should check your blood calcium level when you start and while you are using NATPARA. After you start NATPARA, your healthcare provider may change your doses of calcium and active vitamin D.
- If you miss a day or forget to give your daily NATPARA injection, give your injection as soon as you remember and call your healthcare provider right away. You may need to take more calcium. Take your next dose of NATPARA the next day as prescribed.
- If you use more than your daily dose of NATPARA, call your healthcare provider right away.

What are the possible side effects of NATPARA?

NATPARA may cause serious side effects, including:

- See "What is the most important information I should know about NATPARA?"
- Allergic (hypersensitivity) reaction, including anaphylaxis. Tell your healthcare provider or get emergency medical help right away if you have any of the following symptoms of an allergic reaction:

- swelling of your face, lips, mouth, or tongue
- breathing problems
- fainting, dizziness, feeling lightheaded (low blood pressure)
- fast heartbeat

- itching
- rash
- hives

Do not use NATPARA if you are allergic to parathyroid hormone or any of the ingredients in NATPARA. See the end of this Medication Guide for a complete list of ingredients in NATPARA.

The most common side effects of NATPARA include tingling, tickling, or a burning feeling of your skin (paresthesia), headache and nausea.

These are not all the possible side effects of NATPARA. For more information, ask your doctor. Call your doctor for medical advice about side effects. You may report side effects to FDA at 1-800-FDA-1088.

How should I store NATPARA?

- Unmixed NATPARA medicine cartridges: Refrigerate NATPARA between 36°F to 46°F (2°C to 8°C). Do not freeze.
- Mixed NATPARA medicine cartridges:
  - Refrigerate between 36°F to 46°F (2°C to 8°C). Do not freeze.
  - You can use the Q-Cliq pen for up to 14 days after mixing the medicine cartridge.
  - Throw away the mixed NATPARA medicine cartridges 14 days after mixing the medicine cartridge.
- Store NATPARA away from heat and light.
- Do not freeze or shake NATPARA. Do not use NATPARA if it was frozen or shaken.

Keep NATPARA and all medicines out of the reach of children.

General information about the safe and effective use of NATPARA.

Medicines are sometimes prescribed for purposes other than those listed in a Medication Guide. Do not use NATPARA for a condition for which it was not prescribed. Do not give NATPARA to other people, even if they have the same symptoms you have. It may harm them.

This Medication Guide summarizes the most important information about NATPARA. If you would like more information, talk with your healthcare provider. You can ask your pharmacist or healthcare provider for information about NATPARA that is written for health professionals.

What are the ingredients in NATPARA?

Active ingredient: recombinant human parathyroid hormone

Inactive ingredients: sodium chloride, mannitol, citric acid monohydrate, m-cresol in sterile water

Manufactured by: Takeda Pharmaceuticals U.S.A., Inc., Cambridge, MA 02142, USA
U.S. License Number 1898

NATPARA is a registered trademark of Takeda Pharmaceuticals U.S.A., Inc.

Q-CLIQ is a registered trademark of Takeda Pharmaceuticals U.S.A., Inc.

©2025 Takeda Pharmaceuticals U.S.A., Inc. All rights reserved.

For more information, go to www.NATPARA.com or call 1-800-828-2088.

This Medication Guide has been approved by the U.S. Food and Drug Administration.
Revised: 6/2025

Instructions for Use NATPARA® (nat-PAH-rah) (parathyroid hormone) for injection, for subcutaneous use

Medicine Cartridge Tracker

Instructions:

1. Enter today's date in the space next to "Date Mixed."

2. Enter the date 14 days from today in the "Discard On" section.

3. Dispose of your medicine cartridge on the "Discard On" date even if you have medicine left in the cartridge.

Read this Instructions for Use before you start using NATPARA and each time you get a refill. There may be new information. This information does not take the place of talking to your healthcare provider about your medical condition or your treatment. Before you use NATPARA for the first time, make sure your healthcare provider shows you the right way to use it.

Table of Contents

Getting to Know the Parts of Your Q-Cliq Pen and Your NATPARA Medicine

Preparing and Mixing Your NATPARA

Preparing Your Q-Cliq Pen

Giving Your Daily NATPARA

Frequently Asked Questions

Getting to Know the Parts of Your Q-Cliq Pen and Your NATPARA Medicine

Your Q-Cliq pen can be re-used for up to 2 years. See Figure A.

The rod protector protects the rod during shipment from the factory. Throw away the rod protector when you are ready to use your Q-Cliq pen.

Your NATPARA Medicine Cartridge:

- Your NATPARA medicine cartridge contains medicine powder and a liquid to mix the powder in. See Figure B. You must mix the powder and the liquid in the medicine cartridge before using your Q-Cliq pen.
- Each medicine cartridge contains 14 doses.
- The dose indicator shows you the number of doses left in the medicine cartridge.

Other supplies you will need to give your NATPARA. See Figure C.

- 31G × 8 mm BD Ultra-Fine Pen Needle:
  - The needle is covered with a needle guard
  - The paper tab seals the needle and the needle guard in the needle cap
- puncture-resistant sharps container
- 1 alcohol swab
- mixing device
- NATPARA Medicine Cartridge Tracker (see front cover fold out of your NATPARA booklet)

Preparing and Mixing Your NATPARA

- Mix your NATPARA 1 time every 14 days.
- If this is your first time using NATPARA by yourself, a trainer will guide you through how to mix your first NATPARA medicine cartridge and also your second medicine cartridge.

Step 1. Wash and dry your hands.

Step 2. Gather your supplies, including:

- your Q-Cliq pen
- your mixing device
- new NATPARA medicine cartridge from the refrigerator
- new disposable Pen Needle
- puncture-resistant sharps container
- pencil or pen
- Medicine Cartridge Tracker

Step 3. Look at the Medicine Cartridge Tracker in the front of your NATPARA booklet.

Step 4. Write the date in the space next to "Date Mixed." See Figure D.

Step 5. Write the date 14 days from the day you mixed NATPARA in the space next to "Discard on." This will be the same day of the week 2 weeks later. See Figure E.

- Do not use your NATPARA on or after the "Discard on" date even if there is medicine left in the cartridge.
- Throw away the empty medicine cartridge when it is time to prepare your new cartridge.
- A Pen Needle must be attached to mix a new cartridge.

Step 6. Remove the paper tab from the needle cap. See Figure F.

Step 7. While keeping the needle cap straight, screw it firmly onto the cartridge in a clockwise direction.
Do not remove the needle cap or guard until you are ready to give your medicine. See Figure G.

Step 8. Turn the wheel of the mixing device in a counterclockwise direction to lower the rod if it is not already lowered. See Figure H.

- Make sure the rod in the mixing device looks like this. See Figure I.

Step 9. Screw the cartridge onto your NATPARA mixing device in a clockwise direction. The Pen Needle must be attached. See Figure J.

Step 10. With the needle cap pointing up, turn the wheel slowly in a clockwise direction until the stoppers no longer move. Make sure the wheel turns easily. See Figure K.

Step 11. Make sure the stoppers look like this and stay together. See Figure L.

Step 12. Mix the powder by slowly moving the cartridge back and forth about 10 times.
Do not shake the cartridge. See Figure M.

Step 13. Set the mixing device down with the medicine cartridge attached. Wait until the powder is dissolved and the liquid is colorless, or 5 minutes have passed. It is normal to see small particles in the liquid.

Step 14. If the liquid is colorless, go to Step 15. If the liquid is not colorless, call 1-800-828-2088 for help.

Preparing Your Q-Cliq Pen

You will prepare your Q-Cliq pen 1 time every 14 days

Step 15. Pick up your Q-Cliq pen and remove the cap.
Save the cap for later use. See Figure N.

Step 16. Unscrew the rod protector or the empty medicine cartridge in a counterclockwise direction and throw it away in a puncture-resistant sharps container. See Figure O.

Step 17. Press the injection button. You should see the "0" line up with the notch in the dose window. If you do not see the "0" line up, press the injection button until it is lined up. See Figure P.

Step 18. Lower the rod. If the rod is extended, turn the dark red ring counterclockwise to lower it. Do not tighten the ring too much. See Figure Q.

Step 19. Check the rod. It will have a small space when done the right way. See Figure R.

Step 20. Pick up the mixing device with the needle cap pointing up. Unscrew the cartridge from the mixing device in a counterclockwise direction and set the mixing device down. See Figure S.

Step 21. Attach the medicine cartridge to the pen. Pick up the Q-Cliq pen base and hold it with the rod pointed upright. See Figure T.

Step 22. With the needle cap pointing up, screw the medicine cartridge onto the Q-Cliq pen in a clockwise direction until there is no space between the medicine cartridge and the Q-Cliq pen. See Figure U.

Priming your Q-Cliq pen.

Step 23. Turn the dosage knob until "GO" lines up with the notch in the dose window. See Figure V.

Step 24. Hold the Q-Cliq pen with the needle cap pointing up. See Figure W.

Step 25. Press the injection button on a flat surface, such as a table top, until the "0" lines up with the notch in the dose window. See Figure X.

- It is normal for 1 or 2 drops of liquid to leak out during this step.
- Do not remove the medicine cartridge from the Q-Cliq pen until the "Discard on" date or the medicine cartridge is empty.
- Prime your Q-Cliq pen only 1 time for each new medicine cartridge.

Giving Your Daily NATPARA

- If you have just finished mixing your medicine and preparing your Q-Cliq pen and the Pen Needle is on, go to Step 33.

If you need help at any time, call 1-800-828-2088

Step 26. Wash and dry your hands.

Step 27. Gather your supplies, including:

- your Q-Cliq pen from the refrigerator
- new disposable Pen Needle
- puncture resistant sharps container

Step 28. Remove the cap from the Q-Cliq pen. The mixed medicine cartridge should be inside.

Step 29. Check the medicine inside the cartridge. See Figure Y.

Step 30. If the liquid is colorless, go to Step 31. It is normal to see small particles in the liquid. If the liquid is not colorless, call 1-800-828-2088 for help.

Attaching a new Pen Needle

Step 31. Remove the paper tab from the needle cap. See Figure Z.

Step 32. While keeping the needle cap straight, screw it firmly onto the medicine cartridge in a clockwise direction.
Do not remove the needle cap or needle guard until you are ready to give your NATPARA. See Figure AA.

Step 33. Clean the area of your thigh where you will give NATPARA with an alcohol swab.
Use a different thigh every time you give your NATPARA.
See Figure BB.

Make sure the needle cap is pointing downward at all times during Step 34 to Step 39.

Step 34. Hold the Q-Cliq pen with the needle cap pointing down until after your injection. See Figure CC.

Step 35. Hold the Q-Cliq pen so you can see the dose window. See Figure DD.

Step 36. Turn the dosage knob until "GO" lines up with the notch in the window. Do not turn the dosage knob past "GO." See Figure EE.

- If the dosage knob is hard to turn, you may not have enough liquid left.
  Check the dose indicator on the medicine cartridge to see if there are any doses left or check the "Discard on" date on the Medicine Cartridge Tracker to see if it has been more than 14 days.

Step 37. Gently tap the medicine cartridge 3 to 5 times. See Figure FF.

Prepare the Pen Needle for giving the injection:

Step 38. Pull the needle cap off and set it aside. Make sure you do not unscrew the needle cap. Pull the needle guard off and throw it away. See Figure GG.

Step 39. Hold the Q-Cliq pen so you can see "GO" in the dose window with the Pen Needle pointing down. See Figure HH.

Giving your NATPARA Injection

Step 40. Insert the Pen Needle fully into your thigh. Make sure you can see "GO" in the window. See Figure II.

Step 41. Press the injection button until the "0" lines up with the notch in the dose window. You should see and feel the dosage knob turn back to "0." See Figure JJ.

- Slowly count to 10.
- Keep the Pen Needle in your skin for 10 seconds after pressing the injection button to make sure you get your full dose.

Step 42. Remove the Pen Needle from your skin by pulling it straight out.

- It is normal for 1 or 2 drops of liquid to leak out during this step.
- If you do not think you received your full dose, do not take another dose. Call your healthcare provider. You may need to take calcium and active vitamin D.

Step 43. Carefully put the large needle cap back on the Pen Needle by scooping the cap back on the needle using only 1 hand. See Figure KK.

Step 44. Unscrew the needle cap (with Pen Needle inside) in a counterclockwise direction while holding the medicine cartridge. See Figure LL.

- Do not share your Q-Cliq pen or Pen Needles with anyone else. You may give an infection to them or get an infection from them.

After your injection:

Step 45. Discard your used needles and medicine cartridges

- Put your used needles and medicine cartridges in an FDA-cleared sharps disposal container right away after use. Do not throw away (dispose of) loose needles and medicine cartridges in your household trash. See Figure MM.
- If you do not have an FDA-cleared sharps disposal container, you may use a household container that is:
  - made of a heavy-duty plastic
  - can be closed with a tight-fitting, puncture-resistant lid, without sharps being able to come out
  - upright and stable during use
  - leak-resistant
  - properly labeled to warn of hazardous waste inside the container

- When your sharps disposal container is almost full, you will need to follow your community guidelines for the right way to dispose of your sharps disposal container. There may be state or local laws about how you should throw away used needles. For more information about safe sharps disposal, and for specific information about sharps disposal in the state that you live in, go to the FDA's website at: http://www.fda.gov/safesharpsdisposal.
- Do not dispose of your used sharps disposal container in your household trash unless your community guidelines permit this. Do not recycle your used sharps disposal container.

Step 46. Put the cap back on your Q-Cliq pen

- A medicine cartridge must be attached to the pen before you can put the pen cap on.
- Line up the pocket clip on the cap with the tab on the Q-Cliq pen. See Figure NN.
- Press the cap and Q-Cliq pen together until you hear it click.

Step 47. Put your Q-Cliq pen in the refrigerator.

How should I store NATPARA?

- Unmixed NATPARA medicine cartridges: Refrigerate NATPARA between 36°F to 46°F (2°C to 8°C). Do not freeze.
- Mixed NATPARA medicine cartridges:
  - Refrigerate between 36°F to 46°F (2°C to 8°C). Do not freeze.
  - You can use the Q-Cliq pen for up to 14 days after mixing the medicine cartridge.
  - Throw away the mixed NATPARA medicine cartridges 14 days after mixing the medicine cartridge.
- Store NATPARA away from heat and light.
- Do not freeze or shake NATPARA. Do not use NATPARA if it was frozen or shaken.

Keep NATPARA and all medicines out of the reach of children.

Frequently Asked Questions

There are 4 ways to get your questions answered:

- Call your healthcare provider.
- Visit our Website at www.NATPARA.com.
- Call 1-800-828-2088.
- Find it in the following list of questions.

What does the dose window in the Q-Cliq pen tell me?

The dose window tells you if the Q-Cliq pen is ready for the injection:

- "0" means not ready
- "GO" means ready
- The dose window does not count the number of doses left or given

Why does the dose indicator scale on the medicine cartridge show "14" after I have given an injection using a newly mixed NATPARA medicine cartridge?

You might have forgotten to prime the Q-Cliq pen. See Step 23 in the "Priming your Q-Cliq pen." section of the Instructions for Use. Call 1-800-828-2088 for help.

What if the dosage knob is hard to turn to "GO"?

- Do not use force if the knob will not easily turn to "GO." You may have used your last dose.
- Check the dose indicator on the medicine cartridge to see if there are any doses left, or check the "Discard on" date on the Medicine Cartridge Tracker to see if it has been more than 14 days.
- If the cartridge contains at least 1 dose, call 1-800-828-2088 for help.

What should I do if the NATPARA medicine cartridge is frozen, whether or not it is attached to the Q-Cliq pen?

Throw away the frozen medicine cartridge and mix a new medicine cartridge.

Why do I not throw away the medicine cartridge on day 14 after giving the last injection?

A medicine cartridge or the "dummy" rod protector is needed to put the cap on the Q-Cliq pen. After injecting yourself on day 14, leave the current medicine cartridge on the Q-Cliq pen, put the pen cap back on, and store the pen in the refrigerator. The next day, which will be day 15, throw away the old medicine cartridge and mix a new one.

What if the newly mixed NATPARA medicine cartridge is hard to screw onto the Q-Cliq pen?

- The rod in the Q-Cliq pen may be extended.
- Remove the cartridge and make sure that the rod is fully lowered. If it is not fully lowered, turn the dark red ring to lower it until the ring stops. Do not tighten it too much. Reattach the cartridge and see if it is easier to attach.
- If it is still too hard to screw onto the Q-Cliq pen, check to see if the stoppers in the cartridge window are together.
- If the stoppers are together, call 1-800-828-2088 for help.

What if the stoppers do not stay together after mixing?

- The Pen Needle may not be on correctly.
- Make sure that the Pen Needle is on the right way and that the threads are lined up. Be sure that the needle is firmly attached. You may need to use a new Pen Needle.

What if I have more than a few drops on the tip of the Pen Needle after injection?

This may mean that you did not hold the needle in your thigh for the full 10 seconds. When you give your next scheduled injection, be sure that you hold the needle in your thigh for at least 10 seconds.

What should I do if there are many small bubbles after mixing the NATPARA medicine cartridge?

It is normal to see small air bubbles in the liquid after you finish mixing your NATPARA medicine.

What should I do if the liquid is colored?

Call 1-800-828-2088 for help.

What should I do if the liquid has small particles in it?

It is normal to sometimes see small particles.

How do I clean my Q-Cliq pen and mixing device?

If needed, clean the Q-Cliq pen and mixing device by wiping them with a damp cloth.

Do not place the Q-Cliq pen and mixing device in water, or wash them with any liquid, such as alcohol.

Can I reuse the Pen Needle?

Do not reuse your Pen Needle. You must use a new Pen Needle for each injection.

Manufactured by:
Takeda Pharmaceuticals U.S.A., Inc.
Cambridge, MA 02142
USA
1-800-828-2088

U.S. License Number 1898

NATPARA is a registered trademark of Takeda Pharmaceuticals U.S.A., Inc.

Q-CLIQ is a registered trademark of Takeda Pharmaceuticals U.S.A., Inc.

©2025 Takeda Pharmaceuticals U.S.A., Inc. All rights reserved.

This Instructions for Use has been approved by the U.S. Food and Drug Administration.

Revised: 6/2025

PRINCIPAL DISPLAY PANEL - 25 mcg Cartridge Carton

NDC 68875-0202-2
For subcutaneous use only

Natpara®
(parathyroid hormone)
for Injection

25
mcg/dose

Contains two 14-dose medication
cartridges of Natpara®
(parathyroid hormone) for Injection

Use only after training by a
healthcare provider

- For use with the Mixing Device,
  Q-Cliq® pen, and 31G x 8 mm
  BD Ultra-Fine™ Pen Needles
- See enclosed Full Prescribing
  Information, Medication Guide,
  and Instructions for Use
- Protect from light
- Do not shake or freeze
- Must be refrigerated.
  Store at 36 to 46°F (2 to 8°C)
- Discard mixed solution after 14 days

Rx only

Takeda

PRINCIPAL DISPLAY PANEL - 50 mcg Cartridge Carton

NDC 68875-0203-2
For subcutaneous use only

Natpara®
(parathyroid hormone)
for Injection

50
mcg/dose

Contains two 14-dose medication
cartridges of Natpara®
(parathyroid hormone) for Injection

Use only after training by a
healthcare provider

- For use with the Mixing Device,
  Q-Cliq® pen, and 31G x 8 mm
  BD Ultra-Fine™ Pen Needles
- See enclosed Full Prescribing
  Information, Medication Guide,
  and Instructions for Use
- Protect from light
- Do not shake or freeze
- Must be refrigerated.
  Store at 36 to 46°F (2 to 8°C)
- Discard mixed solution after 14 days

Rx only

Takeda

PRINCIPAL DISPLAY PANEL - 75 mcg Cartridge Carton

NDC 68875-0204-2
For subcutaneous use only

Natpara®
(parathyroid hormone)
for Injection

75
mcg/dose

Contains two 14-dose medication
cartridges of Natpara®
(parathyroid hormone) for Injection

Use only after training by a
healthcare provider

- For use with the Mixing Device,
  Q-Cliq® pen, and 31G x 8 mm
  BD Ultra-Fine™ Pen Needles
- See enclosed Full Prescribing
  Information, Medication Guide,
  and Instructions for Use
- Protect from light
- Do not shake or freeze
- Must be refrigerated.
  Store at 36 to 46°F (2 to 8°C)
- Discard mixed solution after 14 days

Rx only

Takeda

PRINCIPAL DISPLAY PANEL - 100 mcg Cartridge Carton

NDC 68875-0205-2
For subcutaneous use only

Natpara®
(parathyroid hormone)
for Injection

100
mcg/dose

Contains two 14-dose medication
cartridges of Natpara®
(parathyroid hormone) for Injection

Use only after training by a
healthcare provider

- For use with the Mixing Device,
  Q-Cliq® pen, and 31G x 8 mm
  BD Ultra-Fine™ Pen Needles
- See enclosed Full Prescribing
  Information, Medication Guide,
  and Instructions for Use
- Protect from light
- Do not shake or freeze
- Must be refrigerated.
  Store at 36 to 46°F (2 to 8°C)
- Discard mixed solution after 14 days

Rx only

Takeda